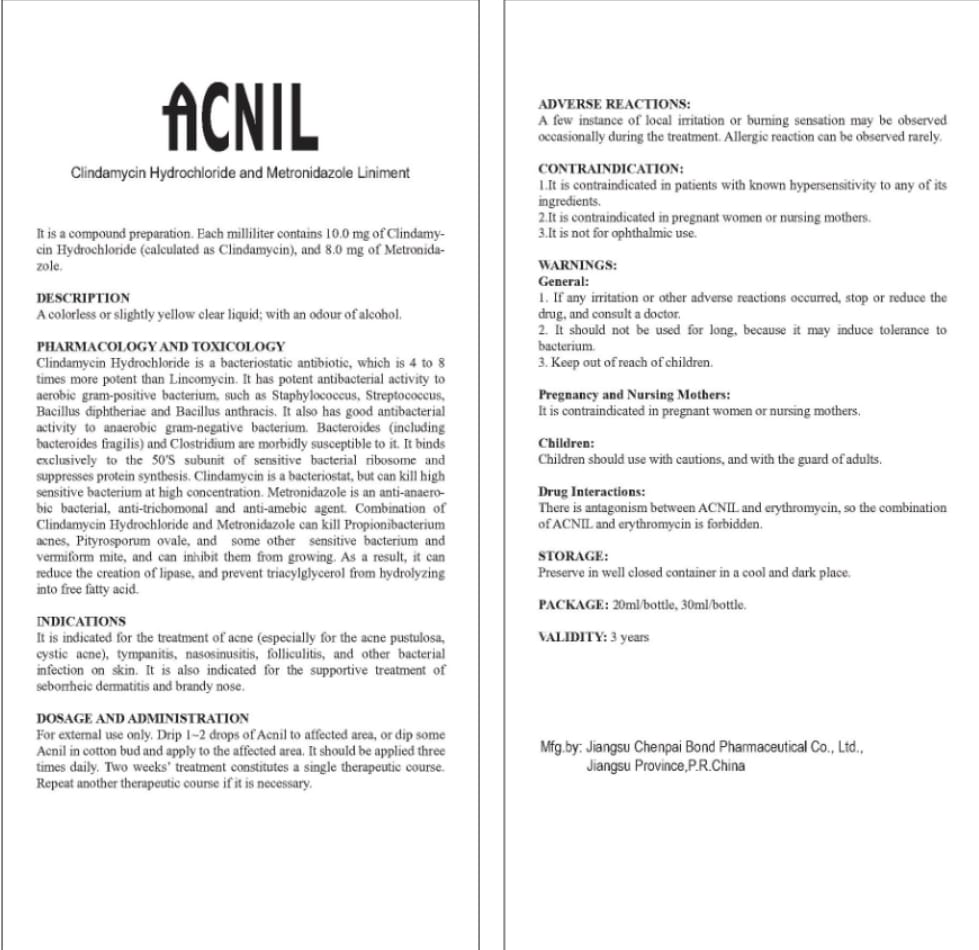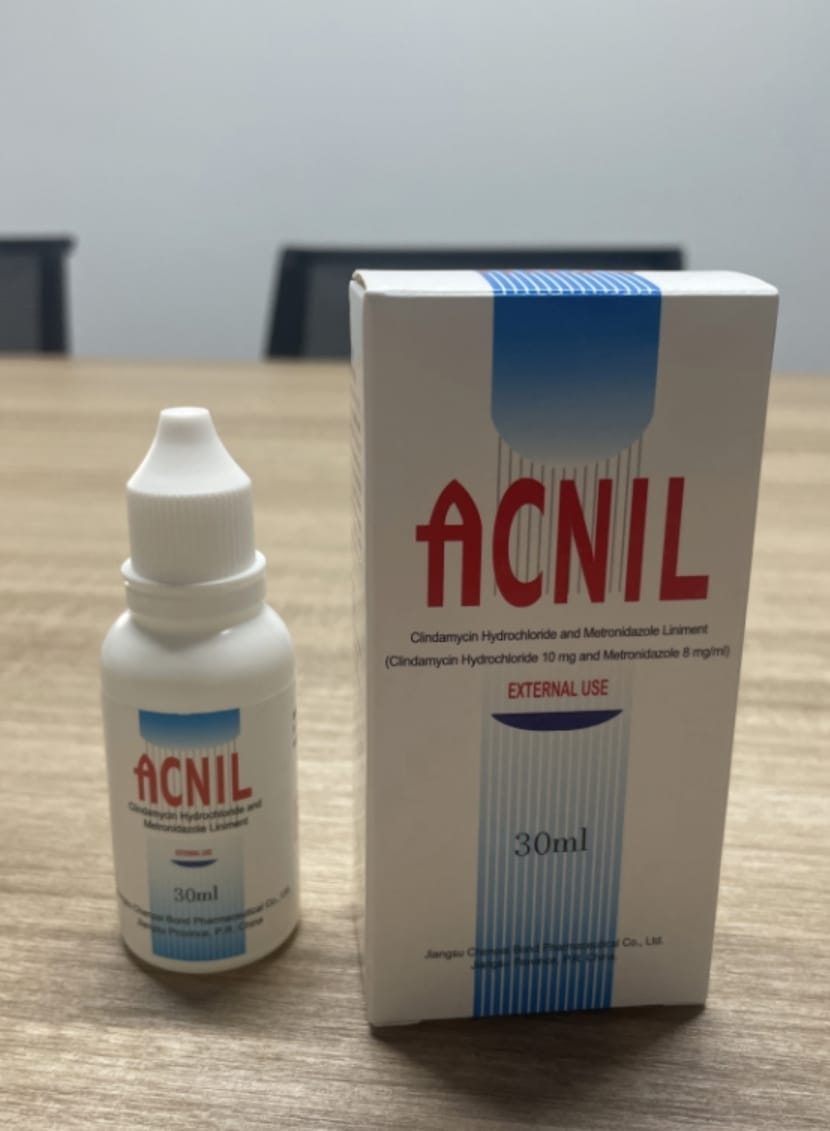 DRUG LABEL: Acnil
NDC: 84277-5647 | Form: LINIMENT
Manufacturer: Jiangsu Chenpai Bond Pharmaceutical Co.,Ltd.
Category: otc | Type: HUMAN OTC DRUG LABEL
Date: 20250217

ACTIVE INGREDIENTS: METRONIDAZOLE 8 mg/30 mL; CLINDAMYCIN HYDROCHLORIDE 10 mg/30 mL
INACTIVE INGREDIENTS: WATER; 2-(ETHYLTHIO)ETHANOL; GLYCEROL FORMAL

DOSAGE AND ADMINISTRATION For external use only. Drip 1~2 drops of Acnil to affected area, or dip some Acnil in cotton bud and apply to the affected area. It should be applied three times daily. Two weeks’ treatment constitutes a single therapeutic course. Repeat another therapeutic course if it is necessary.

WARNINGS

ADVERSE REACTIONS: A few instance of local irritation or burning sensation may be observed. occasionally during the treatment. Allergic reaction can be observed rarely.

INACTIVE INGREDIENT

8.0 mg of Metronidazole.

INDICATIONS AND USAGE

PHARMACOLOGY AND TOXICOLOGY Clindamycin Hydrochloride is a bacteriostatic antibiotic, which is 4 to 8 times more potent than Lincomycin. It has potent antibacterial activity to aerobic gram-positive bacterium, such as Staphylococcus, Streptococcus, Bacillus diphtheriae and Bacillus anthracis. It also has good antibacterial activity to anaerobic gram-negative bacterium. Bacteroides (including bacteroides fragilis) and Clostridium are morbidly susceptible to it. It binds exclusively to the 50'S subunit of sensitive bacterial ribosome and suppresses protein synthesis. Clindamycin is a bacteriostat, but can kill high sensitive bacterium at high concentration. Metronidazole is an anti-anaerobic bacterial, anti-trichomonal and anti-amebic agent. Combination of Clindamycin Hydrochloride and Metronidazole can kill Propionibacterium acnes, Pityrosporum ovale, and some other sensitive bacterium and vermiform mite, and can inhibit them from growing. As a result, it can reduce the creation of lipase, and prevent triacylglycerol from hydrolyzing into free fatty acid.

INDICATIONS It is indicated for the treatment of acne (especially for the acne pustulosa, cystic acne), tympanitis, nasosinusitis, folliculitis, and other bacterial infection on skin. It is also indicated for the supportive treatment of seborrheic dermatitis and brandy nose.

KEEP OUT OF REACH OF CHILDREN

WARNINGS: General: 1. If any irritation or other adverse reactions occurred, stop or reduce the drug, and consult a doctor. 2. It should not be used for long, because it may induce tolerance to bacterium. 3. Keep out of reach of children.

PURPOSE

DESCRIPTION Acolorless or slightly yellow clear liquid; with an odour of alcohol.

PHARMACOLOGY AND TOXICOLOGY Clindamycin Hydrochloride is a bacteriostatic antibiotic, which is 4 to 8 times more potent than Lincomycin. It has potent antibacterial activity to aerobic gram-positive bacterium, such as Staphylococcus, Streptococcus, Bacillus diphtheriae and Bacillus anthracis. It also has good antibacterial activity to anaerobic gram-negative bacterium. Bacteroides (including bacteroides fragilis) and Clostridium are morbidly susceptible to it. It binds exclusively to the 50'S subunit of sensitive bacterial ribosome and suppresses protein synthesis. Clindamycin is a bacteriostat, but can kill high sensitive bacterium at high concentration. Metronidazole is an anti-anaerobic bacterial, anti-trichomonal and anti-amebic agent. Combination of Clindamycin Hydrochloride and Metronidazole can kill Propionibacterium acnes, Pityrosporum ovale, and some other sensitive bacterium and vermiform mite, and can inhibit them from growing. As a result, it can reduce the creation of lipase, and prevent triacylglycerol from hydrolyzing into free fatty acid.

INDICATIONS It is indicated for the treatment of acne (especially for the acne pustulosa, cystic acne), tympanitis, nasosinusitis, folliculitis, and other bacterial infection on skin. It is also indicated for the supportive treatment of seborrheic dermatitis and brandy nose.

Drug Interactions: There is antagonism between ACNIL and erythromycin, so the combination of ACNIL and erythromycin is forbidden.

ACTIVE INGREDIENT

It is a compound preparation. Each milliliter contains 10.0 mg of Clindamycin Hydrochloride (calculated as Clindamycin),

PACKAGE LABEL

Content of Labeling